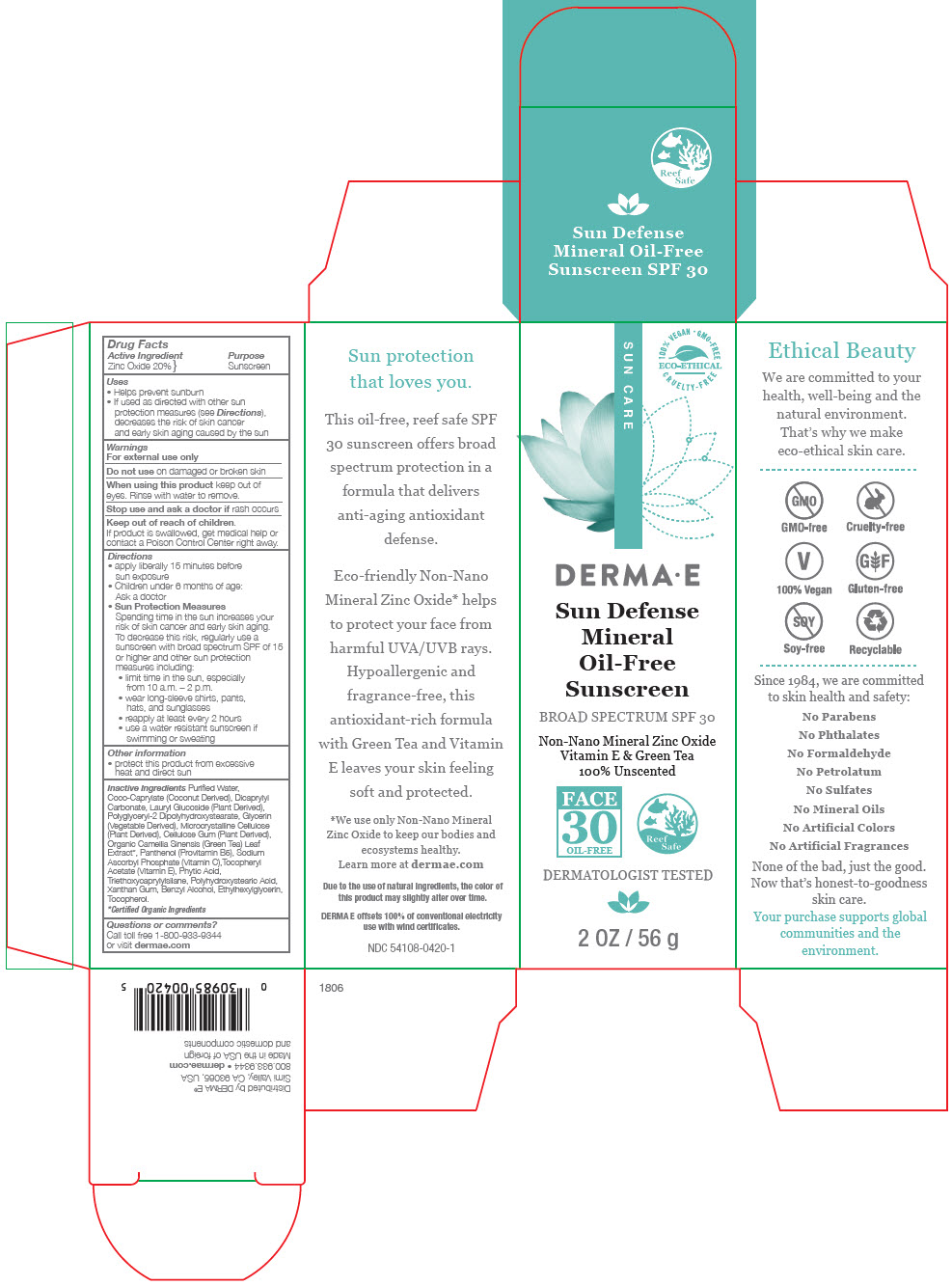 DRUG LABEL: Sun Defense Mineral Sunscreen SPF 30 Face
NDC: 54108-0420 | Form: CREAM
Manufacturer: derma e
Category: otc | Type: HUMAN OTC DRUG LABEL
Date: 20181112

ACTIVE INGREDIENTS: ZINC OXIDE 200 mg/1 g
INACTIVE INGREDIENTS: WATER; COCO-CAPRYLATE; DICAPRYLYL CARBONATE; LAURYL GLUCOSIDE; POLYGLYCERYL-2 DIPOLYHYDROXYSTEARATE; GLYCERIN; MICROCRYSTALLINE CELLULOSE; CARBOXYMETHYLCELLULOSE SODIUM (0.7 CARBOXYMETHYL SUBSTITUTION PER SACCHARIDE; 1200 MPA.S AT 1%); PANTHENOL; SODIUM ASCORBYL PHOSPHATE; .ALPHA.-TOCOPHEROL ACETATE, DL-; FYTIC ACID; TRIETHOXYCAPRYLYLSILANE; POLYHYDROXYSTEARIC ACID (2300 MW); XANTHAN GUM; BENZYL ALCOHOL; ETHYLHEXYLGLYCERIN; TOCOPHEROL

Sun Defense Mineral Sunscreen SPF 30 Face

Drug Facts

Active Ingredient

Zinc Oxide 20%

Purpose

Sunscreen

Uses

- Helps prevent sunburn
- If used as directed with other sun protection measures (see Directions), decreases the risk of skin cancer and early skin aging caused by the sun

Warnings

For external use only

Do not use on damaged or broken skin

When using this product keep out of eyes. Rinse with water to remove.

Stop use and ask a doctor if rash occurs

Keep out of reach of children.

If product is swallowed, get medical help or contact a Poison Control Center right away.

Directions

- apply liberally 15 minutes before sun exposure
- Children under 6 months of age: Ask a doctor
- Sun Protection Measures
  Spending time in the sun increases your risk of skin cancer and early skin aging. To decrease this risk, regularly use a sunscreen with broad spectrum SPF of 15 or higher and other sun protection measures including:
  - limit time in the sun, especially from 10 a.m. – 2 p.m.
  - wear long-sleeve shirts, pants, hats, and sunglasses
  - reapply at least every 2 hours
  - use a water resistant sunscreen if swimming or sweating

Other information

- protect this product from excessive heat and direct sun

Inactive Ingredients

Purified Water, Coco-Caprylate (Coconut Derived), Dicaprylyl Carbonate, Lauryl Glucoside (Plant Derived), Polyglyceryl-2 Dipolyhydroxystearate, Glycerin (Vegetable Derived), Microcrystalline Cellulose (Plant Derived), Cellulose Gum (Plant Derived), Organic Camellia Sinensis (Green Tea) Leaf Extract [Certified Organic Ingredients] , Panthenol (Provitamin B5), Sodium Ascorbyl Phosphate (Vitamin C),Tocopheryl Acetate (Vitamin E), Phytic Acid, Triethoxycaprylylsilane, Polyhydroxystearic Acid, Xanthan Gum, Benzyl Alcohol, Ethylhexylglycerin, Tocopherol.

Questions or comments?

Call toll free 1-800-933-9344 or visit dermae.com

Distributed by DERMA E®
Simi Valley, CA 93065, USA

PRINCIPAL DISPLAY PANEL - 56 g Tube Carton

SUN CARE

100% VEGAN • GMO-FREE
ECO-ETHICAL
CRUELTY-FREE

DERMA•E

Sun Defense
Mineral
Oil-Free
Sunscreen

BROAD SPECTRUM SPF 30

Non-Nano Mineral Zinc Oxide
Vitamin E & Green Tea
100% Unscented

FACE
30
OIL-FREE

Reef
Safe

DERMATOLOGIST TESTED

2 OZ / 56 g